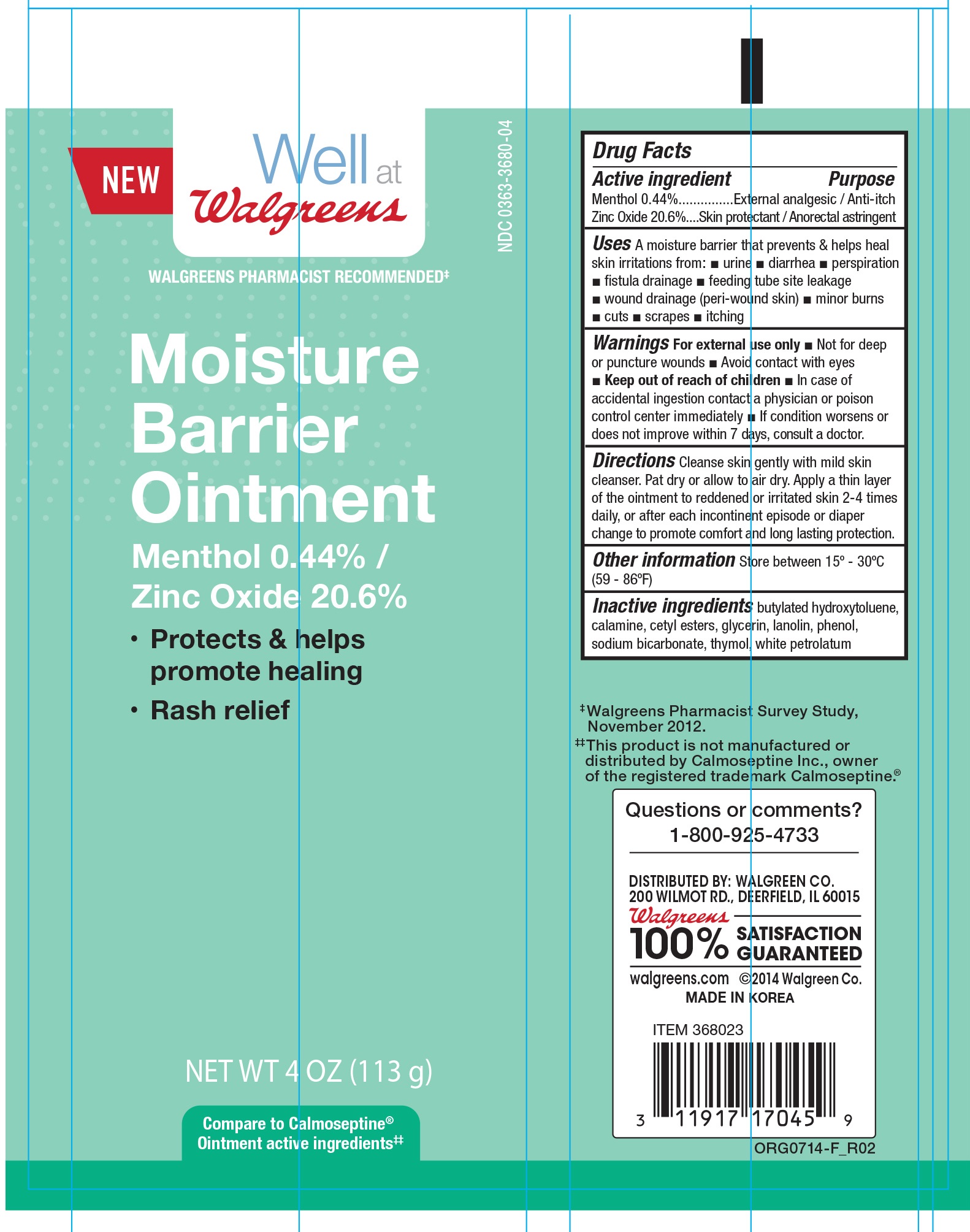 DRUG LABEL: Walgreens Moisture Barrier
NDC: 0363-3680 | Form: CREAM
Manufacturer: Walgreen Company
Category: otc | Type: HUMAN OTC DRUG LABEL
Date: 20260114

ACTIVE INGREDIENTS: MENTHOL 0.44 g/100 g; ZINC OXIDE 20.6 g/100 g
INACTIVE INGREDIENTS: BUTYLATED HYDROXYTOLUENE; CETYL ESTERS WAX; GLYCERIN; LANOLIN; PHENOL; SODIUM BICARBONATE; THYMOL; PETROLATUM

Walgreens Moisture Barrier Ointment 4 oz NBE Calmoseptine

Active ingredients Purpose

Menthol 0.44%......................................................... External analgesic/ Anti-itch

Zinc Oxide 20.6%..................................................... Skin protectant/ Anorectal astringent

Uses

A moisture barrier that prevents & helps heal skin irritations from:

- urine
- diarrhea
- perspiration
- fistula drainage
- feeding tube site leakage
- wound drainage (peri-wound skin)
- minor burns
- cuts
- scrapes
- itching

Warnings:

For external use only

- Not for deep or puncture wounds
- Avoid contact with eyes

Keep out of the reach of children

- In case of accidental ingestion contact a physican or poison control center immediately
- If condition worsens or does not improve within 7 days, consult a doctor

Directions

Cleanse skin gently with mild skin cleanser. Pat dry or allow to air dry. Apply a thin layer of the ointment to irritated skin 2-4 times daily, or after each incontinent episode or diaper change to promote comfort and long lasting protection.

Other information

Store between 15°-30° (59°-86°F)

Inactive ingredients

butylated hydroxytoluene, calamine, cetyl esters, glycerin, lanolin, phenol sodium, bicarbonate, thymol, white petrolatum

DOSAGE AND ADMINISTRATION

DISTRIBUTED BY:

WALGREEN CO.

200 WILMOT RD.

DEERFIELD, IL 60015

MADE IN KOREA